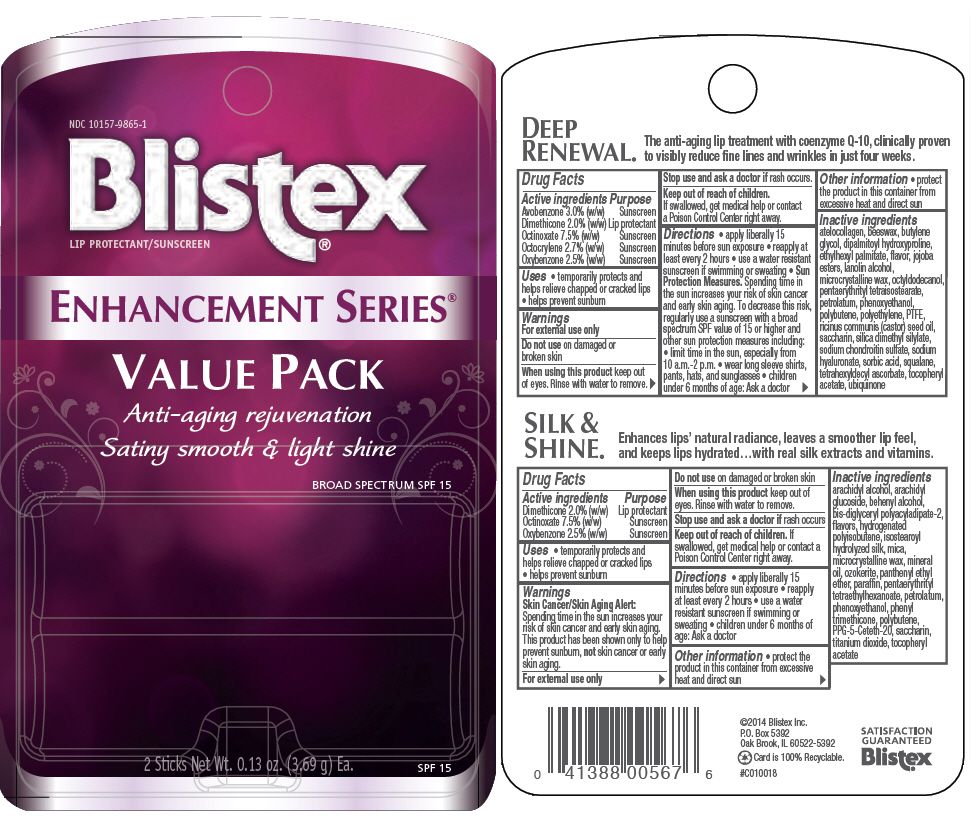 DRUG LABEL: Blistex Enhancement Series (Deep Renewal and Silk and Shine)
NDC: 10157-9865 | Form: KIT | Route: TOPICAL
Manufacturer: Blistex Inc.
Category: otc | Type: HUMAN OTC DRUG LABEL
Date: 20141205

ACTIVE INGREDIENTS: Dimethicone 2 g/100 g; Octinoxate 7.5 g/100 g; Oxybenzone 2.5 g/100 g; Avobenzone 3 g/100 g; Octocrylene 2.7 g/100 g; Dimethicone 2 g/100 g; Octinoxate 7.5 g/100 g; Oxybenzone 2.5 g/100 g
INACTIVE INGREDIENTS: yellow wax; butylene glycol; dipalmitoyl hydroxyproline; ethylhexyl palmitate; lanolin alcohols; microcrystalline wax; octyldodecanol; pentaerythrityl tetraisostearate; petrolatum; phenoxyethanol; high density polyethylene; polytetrafluoroethylene; castor oil; saccharin; silica dimethyl silylate; hyaluronate sodium; sorbic acid; squalane; tetrahexyldecyl ascorbate; Polybutene (1400 MW); MARINE COLLAGEN, SOLUBLE; CHONDROITIN SULFATE SODIUM (SHARK); UBIDECARENONE; SIMMONDSIA CHINENSIS SEED WAX; .alpha.-tocopherol acetate; arachidyl alcohol; arachidyl glucoside; docosanol; mica; microcrystalline wax; mineral oil; panthenyl ethyl ether; paraffin; pentaerythrityl tetraethylhexanoate; petrolatum; phenoxyethanol; phenyl trimethicone; PPG-5-Ceteth-20; saccharin; titanium dioxide; sandalwood; .alpha.-tocopherol acetate; Ceresin; Polybutene (1400 MW)

Blistex® Enhancement Series® (Deep Renewal® and Silk & Shine®)

DEEP RENEWAL®

Drug Facts

ACTIVE INGREDIENT

Active ingredients | Purpose
Avobenzone 3.0% (w/w) | Sunscreen
Dimethicone 2.0% (w/w) | Lip protectant
Octinoxate 7.5% (w/w) | Sunscreen
Octocrylene 2.7% (w/w) | Sunscreen
Oxybenzone 2.5% (w/w) | Sunscreen

Uses

- temporarily protects and helps relieve chapped or cracked lips
- helps prevent sunburn

Warnings

For external use only

Do not use on damaged or broken skin

When using this product keep out of eyes. Rinse with water to remove.

Stop use and ask a doctor if rash occurs.

Keep out of reach of children.

If swallowed, get medical help or contact a Poison Control Center right away.

Directions

- apply liberally 15 minutes before sun exposure
- reapply at least every 2 hours
- use a water resistant sunscreen if swimming or sweating
- Sun Protection Measures. Spending time in the sun increases your risk of skin cancer and early skin aging. To decrease this risk, regularly use a sunscreen with a broad spectrum SPF value of 15 or higher and other sun protection measures including:
  - limit time in the sun, especially from 10 a.m.-2 p.m.
  - wear long sleeve shirts, pants, hats, and sunglasses
- children under 6 months of age: Ask a doctor

Other information

- protect the product in this container from excessive heat and direct sun

Inactive ingredients

atelocollagen, beeswax, butylene glycol, dipalmitoyl hydroxyproline, ethylhexyl palmitate, flavor, jojoba esters, lanolin alcohol, microcrystalline wax, octyldodecanol, pentaerythrityl tetraisostearate, petrolatum, phenoxyethanol, polybutene, polyethylene, PTFE, ricinus communis (castor) seed oil, saccharin, silica dimethyl silylate, sodium chondroitin sulfate, sodium hyaluronate, sorbic acid, squalane, tetrahexyldecyl ascorbate, tocopheryl acetate, ubiquinone

SILK & SHINE®

Drug Facts

ACTIVE INGREDIENT

Active ingredients | Purpose
Dimethicone 2.0% (w/w) | Lip protectant
Octinoxate 7.5% (w/w) | Sunscreen
Oxybenzone 2.5% (w/w) | Sunscreen

Uses

- temporarily protects and helps relieve chapped or cracked lips
- helps prevent sunburn

Warnings

Skin Cancer/Skin Aging Alert

Spending time in the sun increases your risk of skin cancer and early skin aging. This product has been shown only to help prevent sunburn, not skin cancer or early skin aging.

For external use only

Do not use on damaged or broken skin

When using this product keep out of eyes. Rinse with water to remove.

Stop use and ask a doctor if rash occurs

Keep out of reach of children. If swallowed, get medical help or contact a Poison Control Center right away.

Directions

- apply liberally 15 minutes before sun exposure
- reapply at least every 2 hours
- use a water resistant sunscreen if swimming or sweating
- children under 6 months of age: Ask a doctor

Other information

- protect the product in this container from excessive heat and direct sun

Inactive ingredients

arachidyl alcohol, arachidyl glucoside, behenyl alcohol, bis-diglyceryl polyacyladipate-2, flavors, hydrogenated polyisobutene, isostearoyl hydrolyzed silk, mica, microcrystalline wax, mineral oil, ozokerite, panthenyl ethyl ether, paraffin, pentaerythrityl tetraethylhexanoate, petrolatum, phenoxyethanol, phenyl trimethicone, polybutene, PPG-5-Ceteth-20, saccharin, titanium dioxide, tocopheryl acetate

PRINCIPAL DISPLAY PANEL - Kit Blister Pack

NDC 10157-9865-1

Blistex®
LIP PROTECTANT/SUNSCREEN

ENHANCEMENT SERIES®

VALUE PACK
Anti-aging rejuvenation
Satiny smooth & light shine

BROAD SPECTRUM SPF 15

2 Sticks Net Wt. 0.13 oz. (3.69 g) Ea.

SPF 15